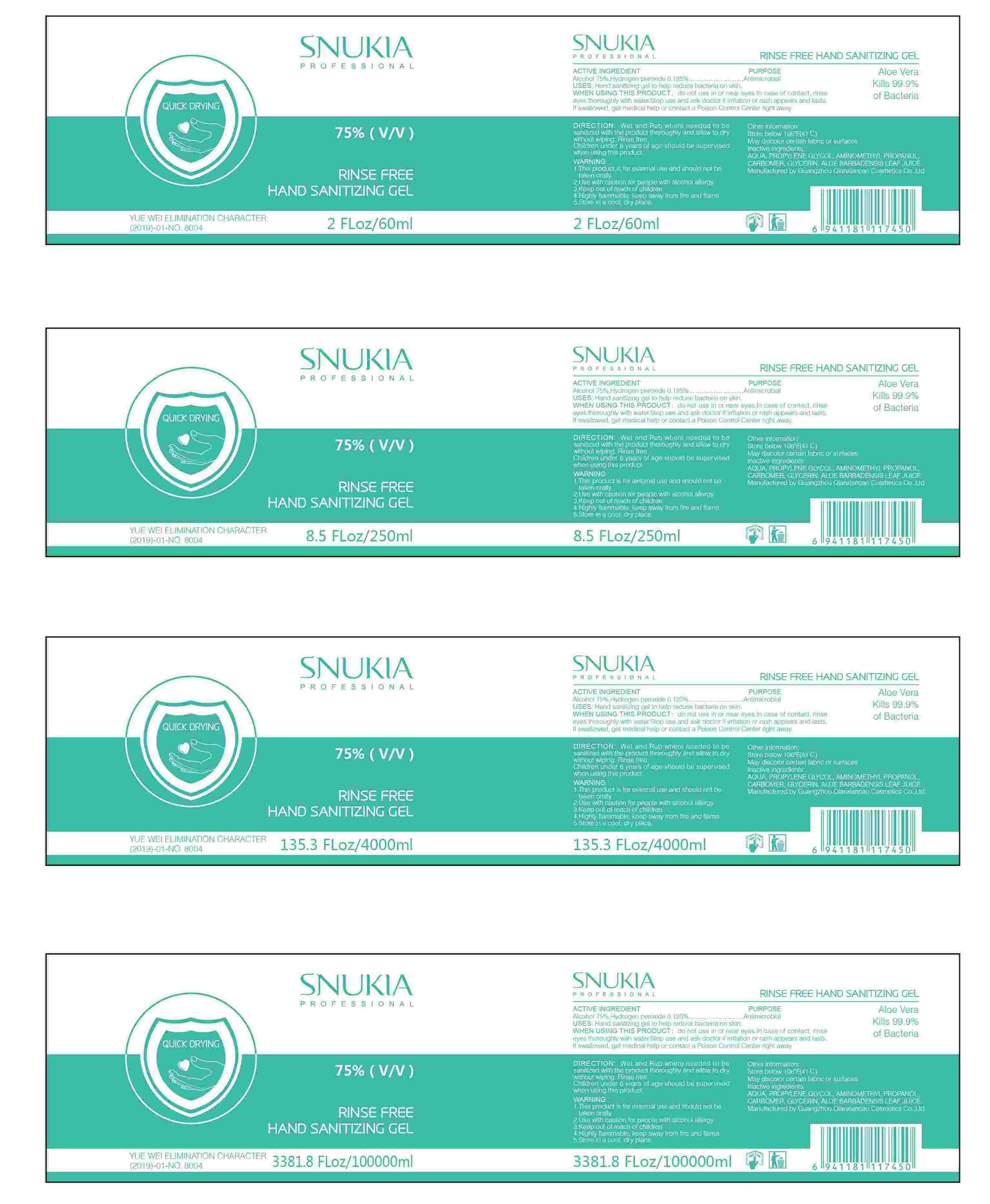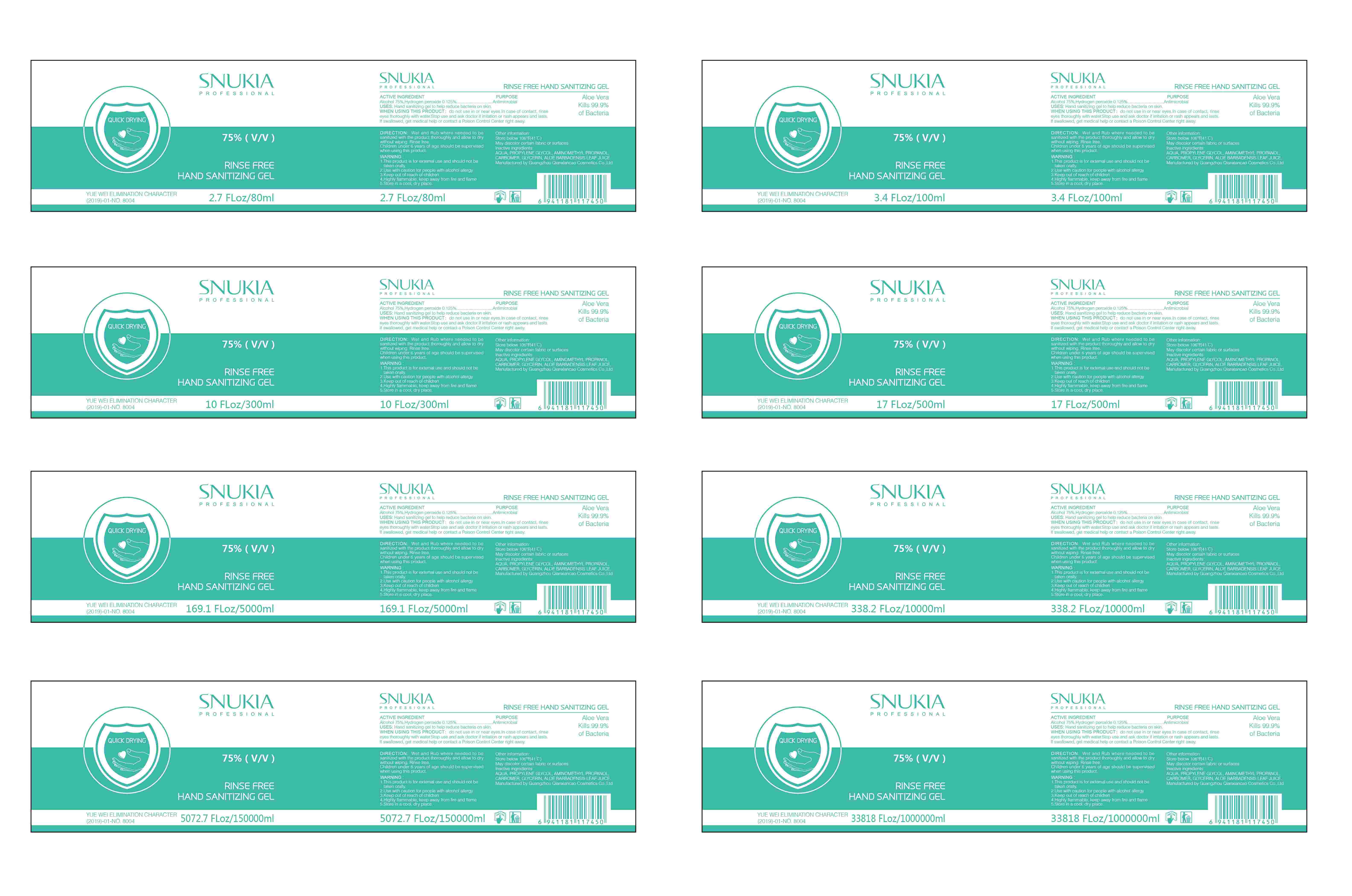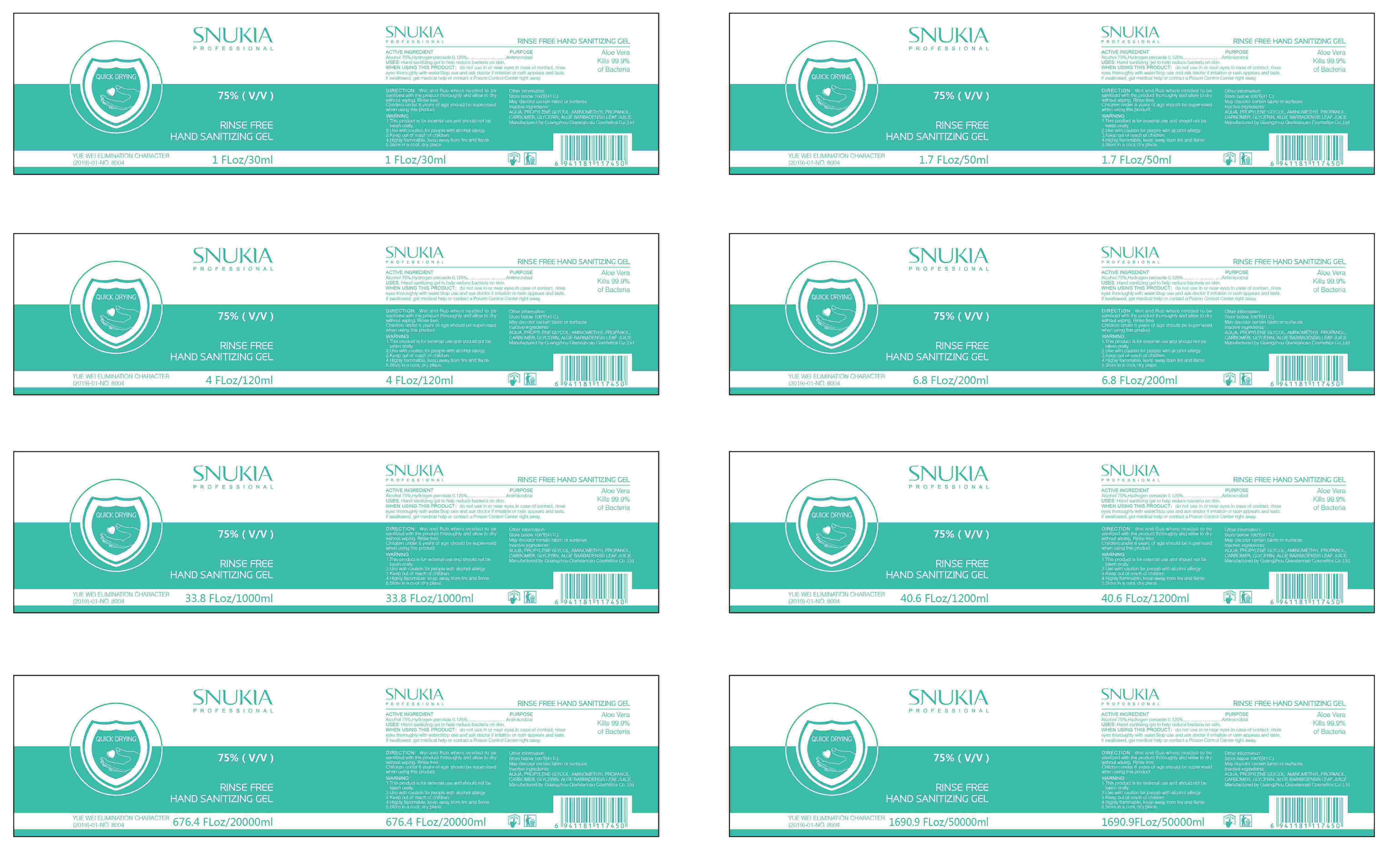 DRUG LABEL: Rinse free hand sanitizing gel
NDC: 78963-006 | Form: GEL
Manufacturer: Guangzhou Qianxiancao Cosmetics Co.,Ltd.
Category: otc | Type: HUMAN OTC DRUG LABEL
Date: 20200729

ACTIVE INGREDIENTS: ALCOHOL 75 mL/100 mL; HYDROGEN PEROXIDE 0.125 mL/100 mL
INACTIVE INGREDIENTS: AMINOMETHYLPROPANOL; PROPYLENE GLYCOL; WATER; CARBOMER HOMOPOLYMER, UNSPECIFIED TYPE; ALOE VERA LEAF; GLYCERIN

RINSE FREE HAND SANITIZING GEL

Active Ingredient(s)

Alcohol 75% ,Hydrogen peroxide 0.125%

Purpose

Antiseptic, Hand Sanitizer

Use

Hand sanitizinggel to help reduce bacteria on skin.

Warnings

WarningI This product is for external use and should not be takenorally

2. Use with caution for people with alcohol allergy

3. Keep out of reach of children

4. Highly flammable, keep away from fire and flame

5. Store in a cool, dry placeWhen using this produet, do not use in or near eyes. Incase of contact, rinse eyes thoroughly with water. Stopuse and ask doctor if irritation or rash appears and lastsIf swallowed, get medical help or contact a Poison ControlCenter right away

Do not use

/

when using this product, do not use in or near eyes. Incase of contact, rinse eyes thoroughly with water. Stopuse and ask doctor if irritation or rash appears and lastsIf swallowed, get medical help or contact a Poison ControlCenter right away.

Stop use and ask a doctor if irritation or rash occurs. These may be signs of a serious condition.

Keep out of reach of children. If swallowed, get medical help or contact a Poison Control Center right away.

Directions

Direction: Wet and Rub where needed to be sanitizedwith the product thoroughly and allow to dry withoutwiping.

Rinse free.Children under 6 years of age should be supervised whenusing this product.

Other information

- Other information:Store below 106F(41 C)May discolor certain fabric or surfaces

Inactive ingredients

AQUA, PROPYLENE GLYCOL , AMINOMETHYL PROPANOL,

CARBOMER, GLYCERIN, ALOE BARBADENSIS LEAF JUICE